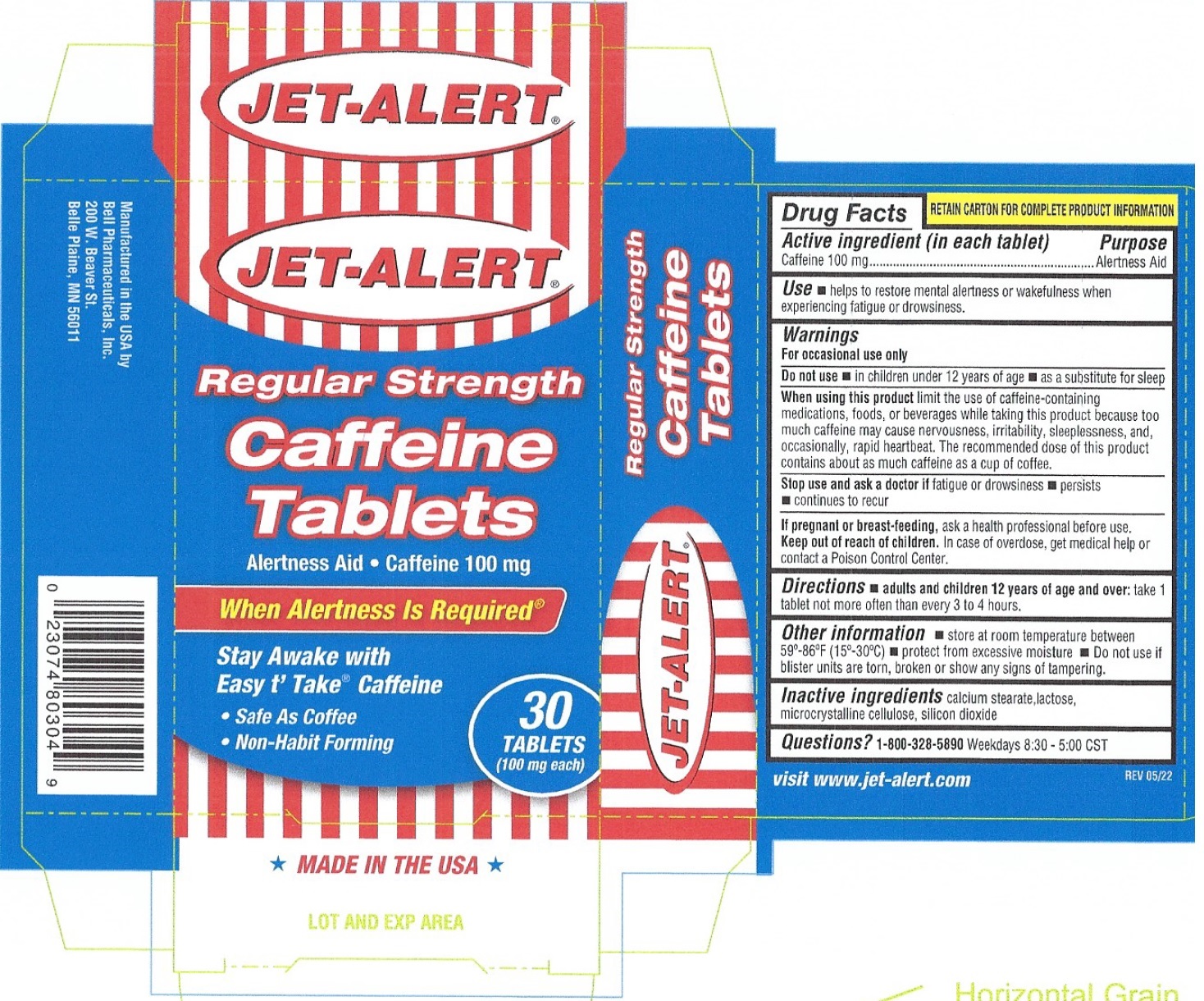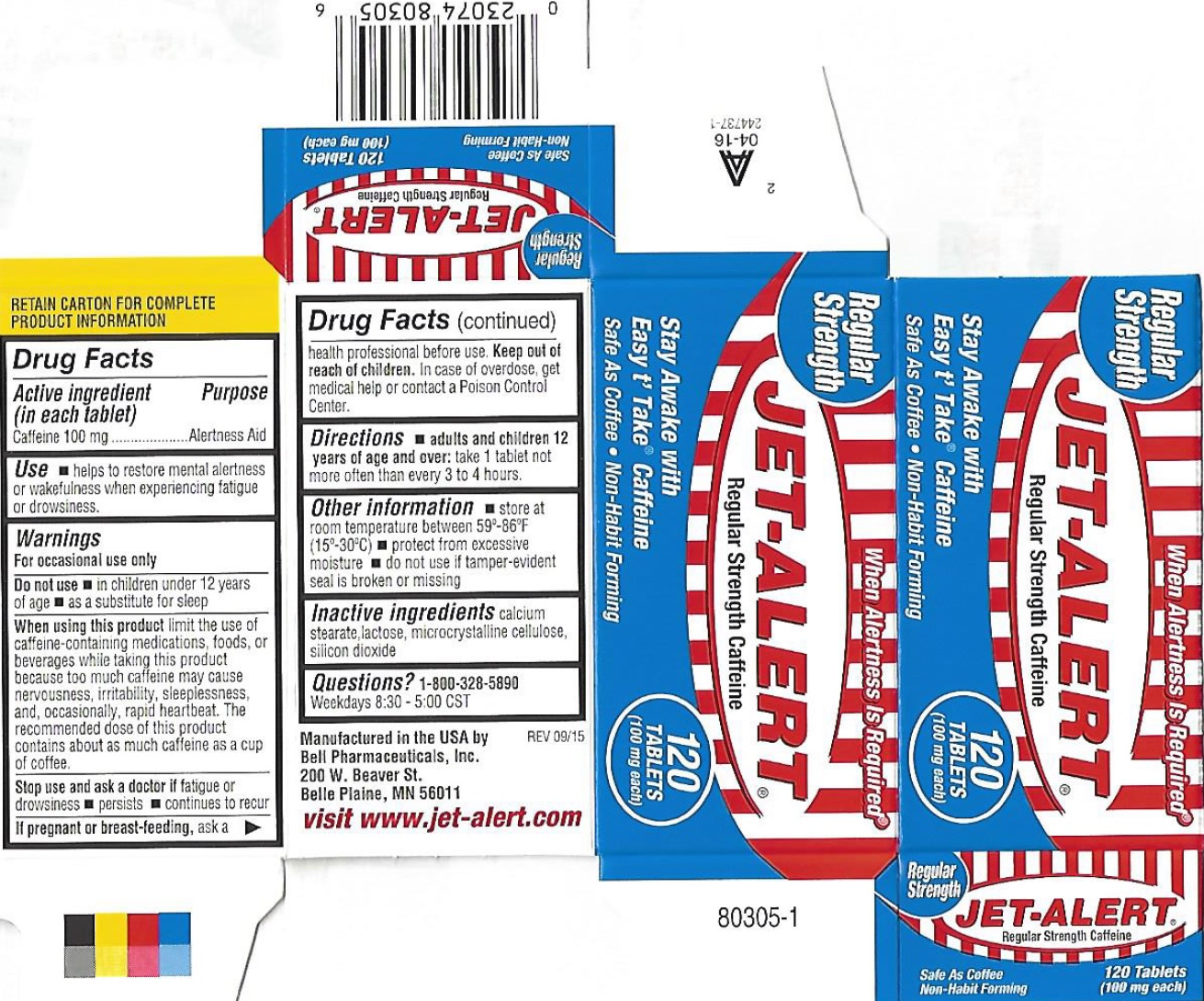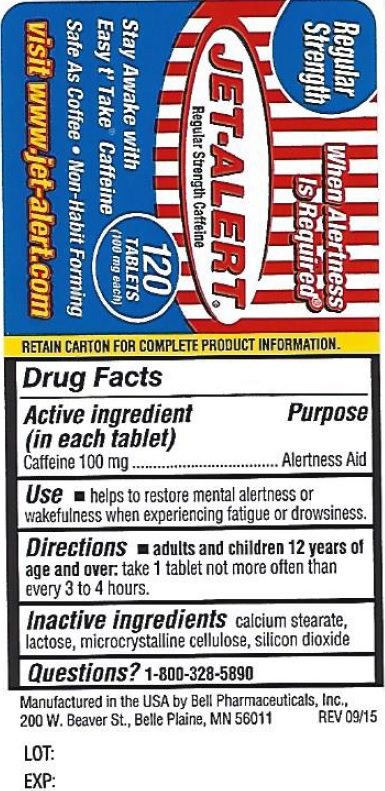 DRUG LABEL: JET ALERT Regular Strength
NDC: 15579-201 | Form: TABLET, COATED
Manufacturer: Bell Pharmaceuticals, Inc
Category: otc | Type: HUMAN OTC DRUG LABEL
Date: 20231215

ACTIVE INGREDIENTS: CAFFEINE 100 mg/1 1
INACTIVE INGREDIENTS: CALCIUM STEARATE; LACTOSE; CELLULOSE, MICROCRYSTALLINE; SILICON DIOXIDE

JET-ALERT Regular Strength

Active ingredient (in each tablet)

Caffeine 100 mg

Purpose

Alertness Aid

Uses

helps to restore mental alertness or wakefulness when experiencing fatigue or drowsiness.

Warnings

For occasional use only

Do not use

• in children under 12 years of age • as a substitute for sleep

When using this product

Limit the use of caffeine-containing medications, foods, or beverages while taking this product because too much caffeine may cause nervousness, irritability, sleeplessness, and, occasionally, rapid heartbeat. The recommended dose of this product contains about as much caffeine as a cup of coffee.

Stop use and ask a doctor if

fatigue or drowsiness • persists • continues to recur

If pregnant or breast-feeding,

ask a health professional before use.

Keep out of reach of children.

In case of overdose, get medical help or contact a Poison Control Center.

Directions

take 1 tablet not more often than every 3 to 4 hours. • adults and children 12 years of age and over:

Other information

• store at room temperature between 59°-86°F (15°-30°C) • protect from excessive moisture • do not use if tamper-evident seal is broken or missing

Inactive ingredients

calcium stearate, lactose, microcrystalline cellulose, silicon dioxide.

Questions?

1-800-328-5890

Weekdays 8:30-5:00 CST